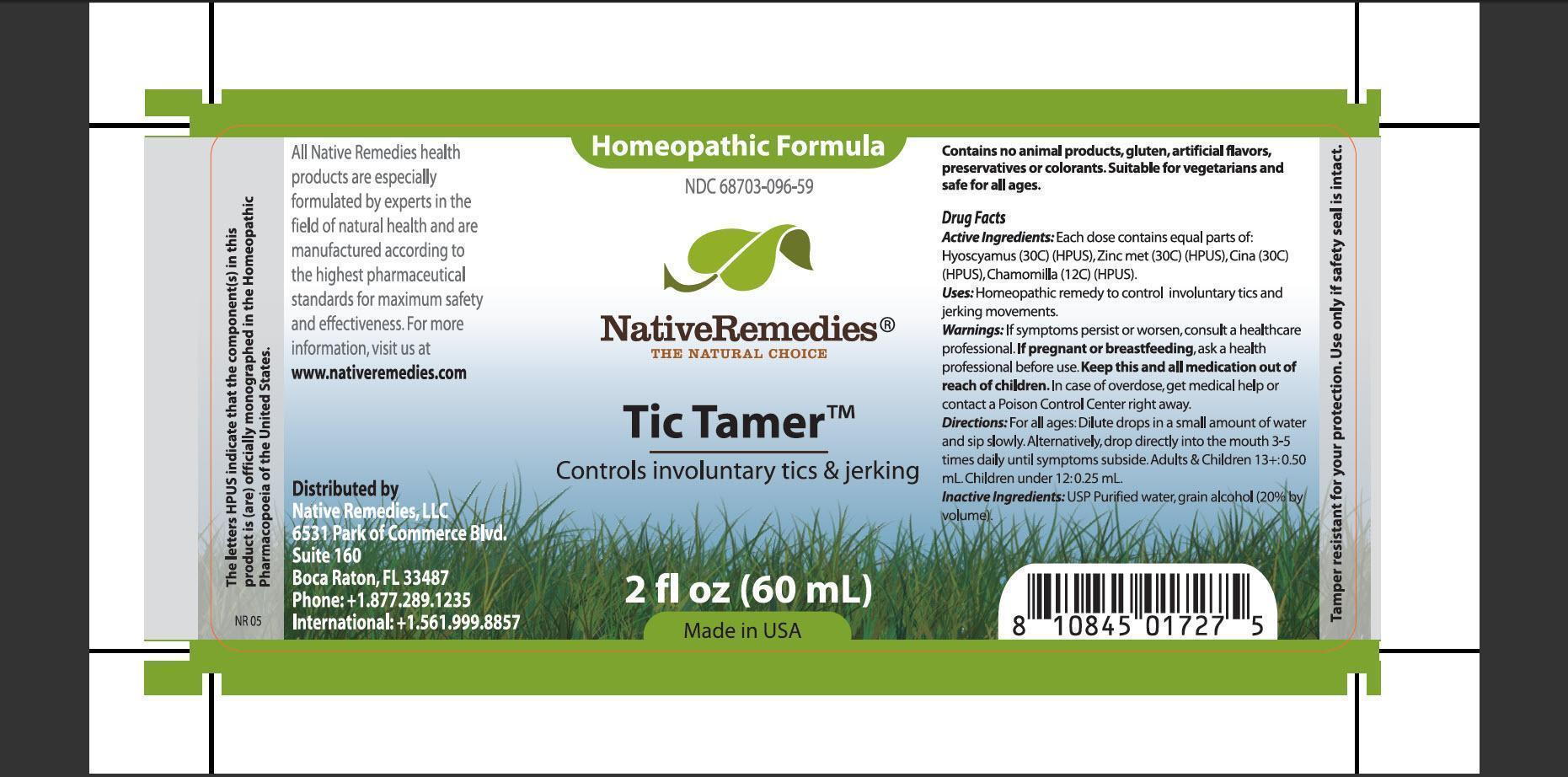 DRUG LABEL: Tic Tamer
NDC: 68703-096 | Form: TINCTURE
Manufacturer: Native Remedies, LLC
Category: homeopathic | Type: HUMAN OTC DRUG LABEL
Date: 20130329

ACTIVE INGREDIENTS: HYOSCYAMUS NIGER 30 [hp_C]/1 mL; ZINC 30 [hp_C]/1 mL; ARTEMISIA CINA PRE-FLOWERING TOP 30 [hp_C]/1 mL; MATRICARIA RECUTITA 12 [hp_C]/1 mL
INACTIVE INGREDIENTS: WATER; ALCOHOL

Tic Tamer

PURPOSE

Controls involuntary tics and jerking

ACTIVE INGREDIENT

Active Ingredients: Each dose contains equal parts of: Hyoscyamus (30C) (HPUS), Zinc met (30C) (HPUS), Cina (30C) (HPUS), Chamomilla (12C) (HPUS)

INDICATIONS AND USAGE

Uses:Homeopathic remedy to control involuntary tics and jerking movements

WARNINGS

Warnings: If symptoms persist or worsen, consult a healthcare professional

PREGNANCY OR BREAST FEEDING

If pregnant of breastfeeding, ask a health professional before use

KEEP OUT OF REACH OF CHILDREN

Keep this and all medication out of reach of children

OVERDOSAGE

In case of overdose, get medical help or contact a Poison Control Center right away

DOSAGE AND ADMINISTRATION

Directions: For all ages: Dilute drops in a small amount of water and sip slowly. Alternatively, drop directly into the mouth 3-5 times daily until symptoms subside. Adults and children 13+: 0.50 mL. Children under 12: 0.25 mL

INACTIVE INGREDIENT

Inactive Ingredients: USP Purified water, grain alcohol (20% by volume)

PATIENT COUNSELING INFORMATION

The letters HPUS indicate that the component(s) in this product is (are) officially monographed in the Homeopathic Pharmacopoeia of the United States

All Native Remedies health products are especially formulated by experts in the field of natural health and are manufactured according to the highest pharmaceutical standards for maximum safety and effectiveness. For more information, visit us at www.nativeremedies.com

Distributed by
Native Remedies, LLC
6531 Park of Commerce Blvd.
Suite 160
Boca Raton, FL 33487
Phone: +1.877.289.1235
International:+1.561.999.8857

Contains no animal products, gluten, artificial flavors, preservatives or colorants. Suitable for vegetarians and safe for all ages

STORAGE AND HANDLING

Tamper resistant for your protection. Use only if safety seal is intact